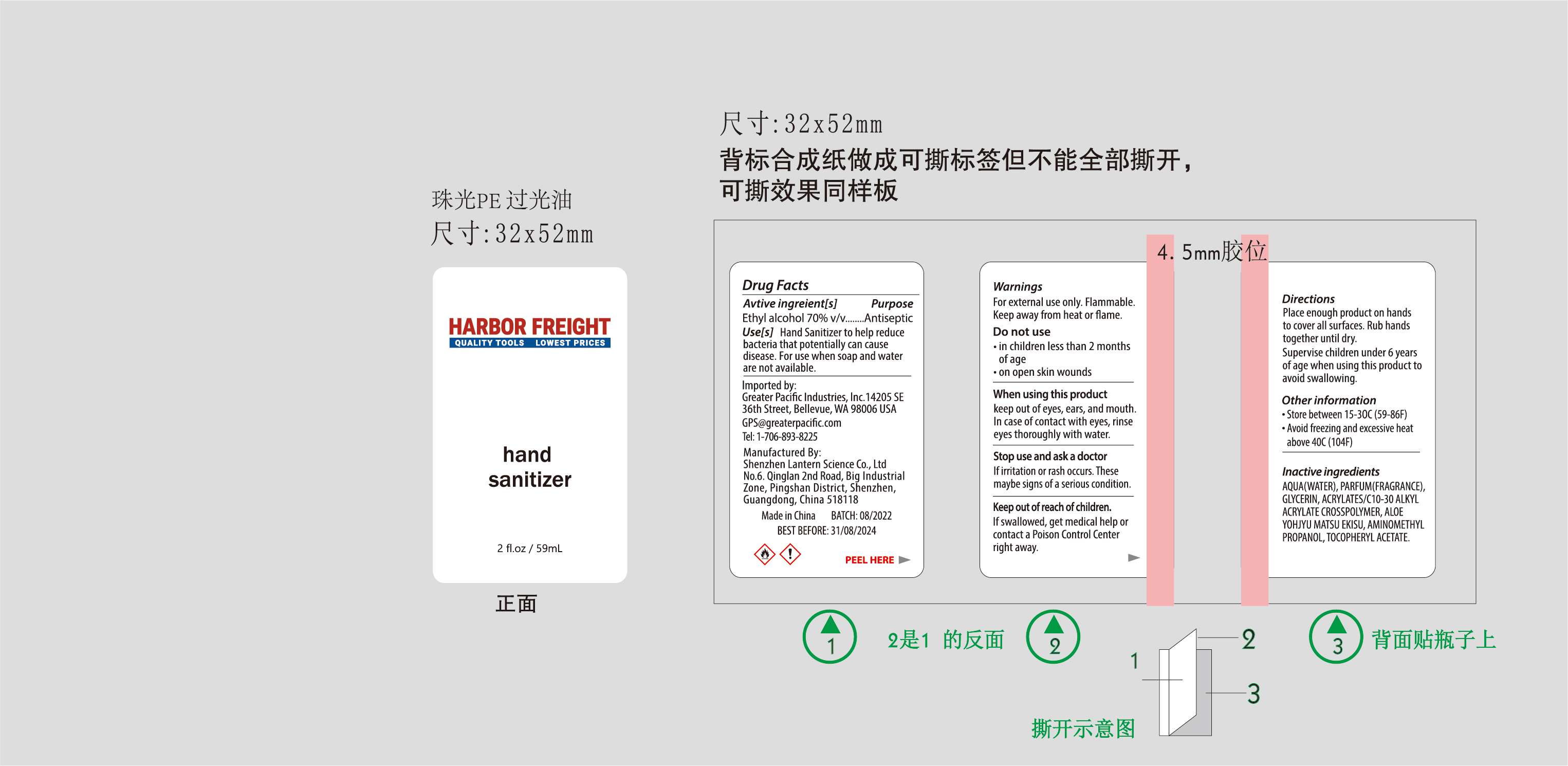 DRUG LABEL: HARBOR FREIGHT Hand sanitizer 59mL
NDC: 54860-397 | Form: GEL
Manufacturer: Shenzhen Lantern Science Co.,Ltd
Category: otc | Type: HUMAN OTC DRUG LABEL
Date: 20220726

ACTIVE INGREDIENTS: ALCOHOL 70 mL/100 mL
INACTIVE INGREDIENTS: ALOE VERA LEAF 0.1 mL/100 mL; ALOE 0.05 mL/100 mL; CARBOMER COPOLYMER TYPE A 0.3 mL/100 mL; WATER 28.949 mL/100 mL; AMINOMETHYLPROPANOL 0.1 mL/100 mL; GLYCERIN 0.5 mL/100 mL; .ALPHA.-TOCOPHEROL ACETATE 0.001 mL/100 mL

HARBOR FREIGHT Hand sanitizer 59mL

Active Ingredient

Active Ingredients Purpose

Ethyl Alcohol 70% Antiseptic

Use

the hand sanitizer to help reduce bacteria that potentially can cause disease,For use when soap and water are not available.

DOSAGE AND ADMINISTRATION

Recommended for repeated use.

use anywhere without water.

Warning

For external use only,Flammable,keep away from heat or flame.

WARNINGS AND PRECAUTIONS

For external use only.

Flammable, keep away from heat and flame.

STOP USE

Discontinue if skin becomes irritated and ask a doctor .

Keep out of reach of children. In case of accidental ingestion, seek professional assistance or contact a poson control center immediately.

Inactive ingredients

water,Glycerin,Acrylates/C10-30 Alkyl Acrylate Crosspolymer,Aminomethyl Propanol,Parfum,Aloe Yohjyu Matsu Ekisu,Tocopheryl Acetate.

Directions

place enough product on hands to cover all surfaces.rub hands together until dry.

supervise children under 6 years of age when using this product to avoid swallowing.

When using this product

keep out of eyes. In case of contact with eyes, flush thoroughly with water.

Do not inhale or ingest.

Avoid contact with broken skin.

Other information

Do not store above 105F.

May discolor some fabrics.

Harmful to wood finishes and plastics.

When using this product

Keep out of eyes,ears,and mouth.In case of contact with eyes,rinse eyes thotoughly with water.

OTHER SAFETY INFORMATION

Store between 15-30℃（59-86F）

Avoid freezing and excessive heat above 40℃（104F）

DO NOT USE

in children less than 2 months of age

on open skin wounds

Stop use and ask a doctor

If irritation or rash occurs,these maybe signs of a serious condition.

Keep out of reach of children

If swallowed,get medical help or contact a Poison control center right away.